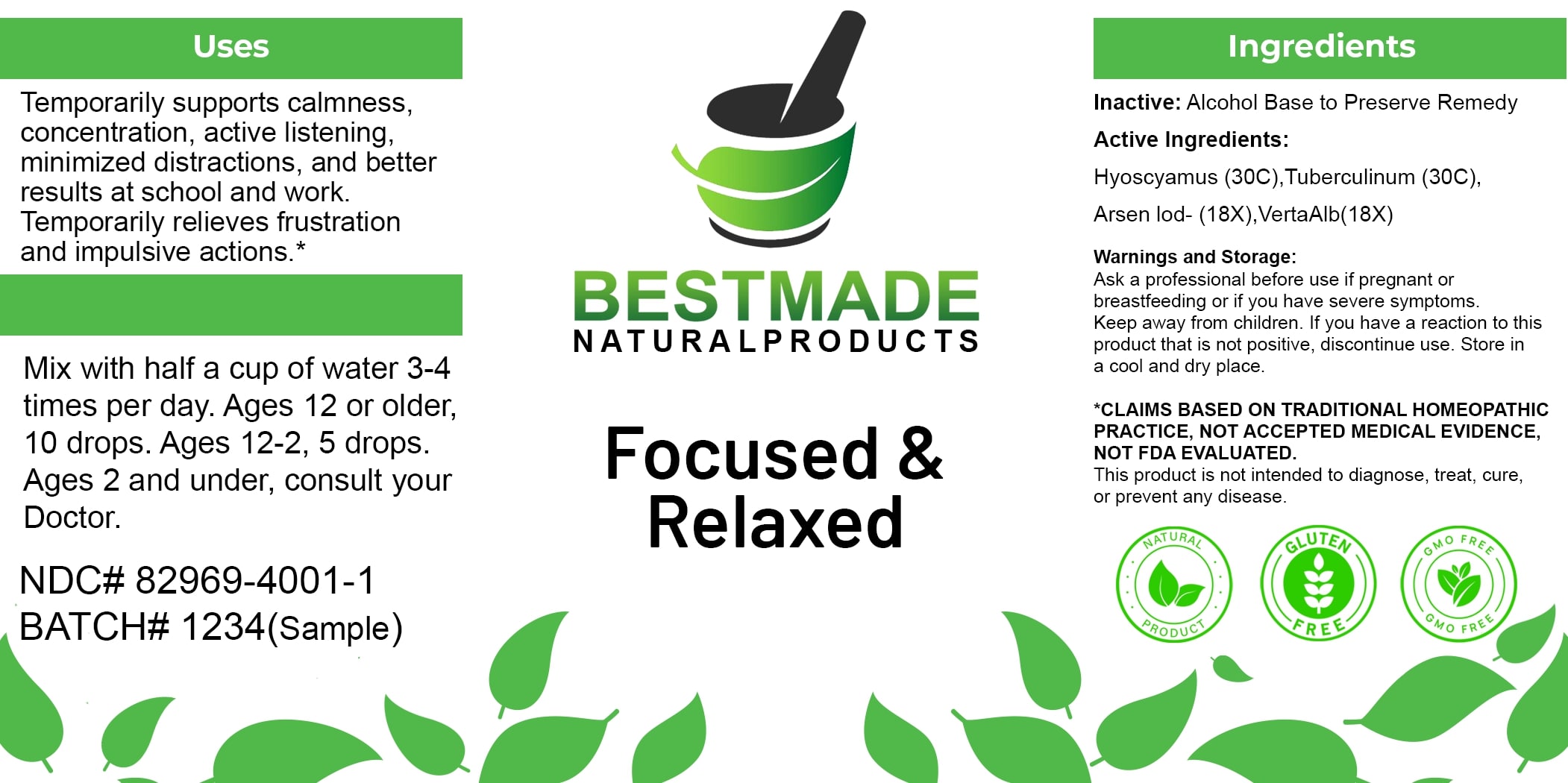 DRUG LABEL: Bestmade Natural Products Focused and Relaxed
NDC: 82969-4001 | Form: LIQUID
Manufacturer: Bestmade Natural Products
Category: homeopathic | Type: HUMAN OTC DRUG LABEL
Date: 20250307

ACTIVE INGREDIENTS: ARSENIC TRIIODIDE 30 [hp_C]/30 [hp_C]; VERATRUM ALBUM ROOT 30 [hp_C]/30 [hp_C]; TUBERCULIN PURIFIED PROTEIN DERIVATIVE 30 [hp_C]/30 [hp_C]; HYOSCYAMUS NIGER 30 [hp_C]/30 [hp_C]
INACTIVE INGREDIENTS: ALCOHOL 30 [hp_C]/30 [hp_C]

Focused & Relaxed

DOSAGE AND ADMINISTRATION

How to Use

Mix with half a cup of water 3-4 times per day. Ages 12 or older, 10 drops. Ages 12-2, 5 drops. Ages 2 and under, consult your Doctor.

INACTIVE INGREDIENT

Ingredients

Inactive: Alcohol Base to Preserve Remedy

ACTIVE INGREDIENT

Active Ingredients: Hyoscyamus (30C), Tuberculinum (30C), Arsen Iod (18X), Verta Alb (18X)

Uses

Temporarily supports calmness, concentration, active listening, minimized distractions, and better results at school and work. Temporarily relieves frustration and impulsive actions.*

*CLAIMS BASED ON TRADITIONAL HOMEOPATHIC PRACTICE, NOT ACCEPTED MEDICAL EVIDENCE, NOT FDA EVALUATED.

This product is not intended to diagnose, treat, cure, or prevent any disease.

Uses

Temporarily supports calmness, concentration, active listening, minimized distractions, and better results at school and work. Temporarily relieves frustration and impulsive actions.*

*CLAIMS BASED ON TRADITIONAL HOMEOPATHIC PRACTICE, NOT ACCEPTED MEDICAL EVIDENCE, NOT FDA EVALUATED.

This product is not intended to diagnose, treat, cure, or prevent any disease.

KEEP OUT OF REACH OF CHILDREN

Warnings and Storage:

Ask a professional before use if pregnant or breastfeeding or if you have severe symptoms. Keep away from children. If you have a reaction to this product that is not positive, discontinue use. Store in a cool and dry place.

Warnings and Storage:

Ask a professional before use if pregnant or breastfeeding or if you have severe symptoms. Keep away from children. If you have a reaction to this product that is not positive, discontinue use. Store in a cool and dry place.

*CLAIMS BASED ON TRADITIONAL HOMEOPATHIC PRACTICE, NOT ACCEPTED MEDICAL EVIDENCE, NOT FDA EVALUATED.

This product is not intended to diagnose, treat, cure, or prevent any disease.

Entire package label